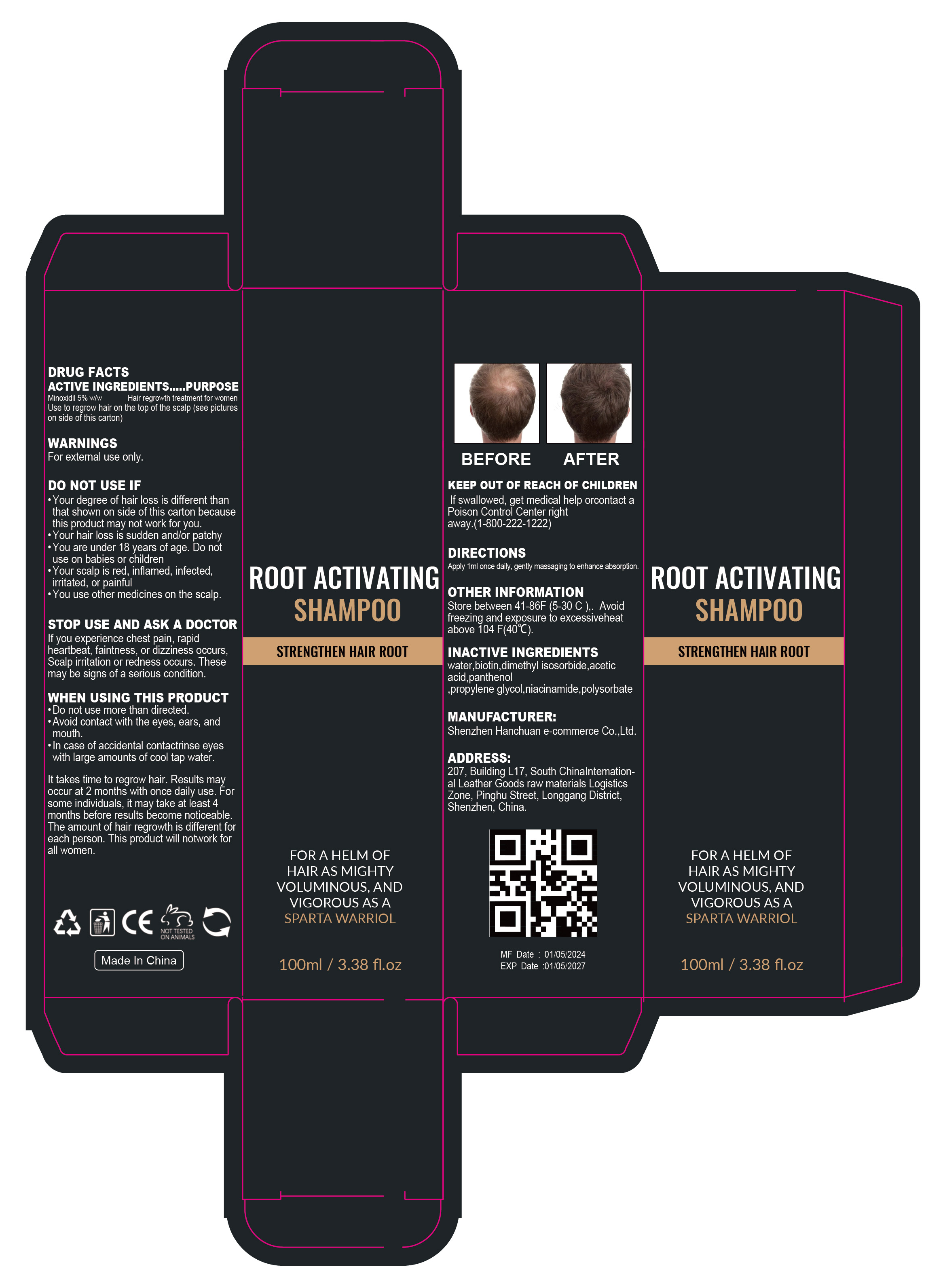 DRUG LABEL: ROOT ACTIVATING SHAMPOOS
NDC: 84302-005 | Form: LIQUID
Manufacturer: Shenzhen Hanchuan e-commerce Co., Ltd
Category: otc | Type: HUMAN OTC DRUG LABEL
Date: 20240515

ACTIVE INGREDIENTS: MINOXIDIL 5 g/100 mL
INACTIVE INGREDIENTS: POLYSORBATE 80; PANTHENOL; ACETIC ACID; PROPYLENE GLYCOL; BIOTIN; NIACINAMIDE; WATER; DIMETHYL ISOSORBIDE

Root Activating Shampoo

ACTIVE INGREDIENT

Minoxidil 5%

PURPOSE

Hair regrowth treatment for women Use to regrow hair on the top of the scalp

KEEP OUT OF REACH OF CHILDREN

lf swallowed, get medical help orcontact a Poison Control Center rightaway.(1-800-222-1222)

INDICATIONS AND USAGE

ROOT ACTIVATING SHAMPOO STRENGTHEN HAIR ROOT
FORAHELM OF HAIR AS MIGHTY VOLUMINOUS，AND VIGOROUS AS A SPARTA WARRIOL

WARNINGS

For external use only

DO NOT USE

Your degree of hair loss is different than that shown on side of this carton because this product may not work for you.
Your hair loss is sudden and/or patchy.
You are under 18 years of age. Do not use on babies or children.
Your scalp is red, inflamed, infected.irritated, or painful.
You use other medicines on the scalp.

STOP USE

if you experience chest pain, rapidheartbeat, faintness, or dizziness occursScalp irritation or redness occurs. Thesemay be signs of a serious condition.

Do not use more than directed.
Avoid contact with the eyes, ears, and mouth.
In case of accidental contactrinse eyeswith large amounts of cool tap water.

DOSAGE AND ADMINISTRATION

lt takes time to regrow hair. Results mayoccur at 2 months with once daily use. Forsome individuals, it may take at least 4months before results become noticeable.The amount of hair regrowth is different foreach person. This product will notwork forall women.

Apply 1ml once daily, gently massaging to enhance absorption

STORAGE AND HANDLING

Store between 41-86F (5-30 C). Avoid freezing and exposure to excessiveheat above 104 F(40°C)

INACTIVE INGREDIENT

water
biotin
dimethyl isosorbide
acetic acid
panthenol
propylene glycol
niacinamide
polysorbate